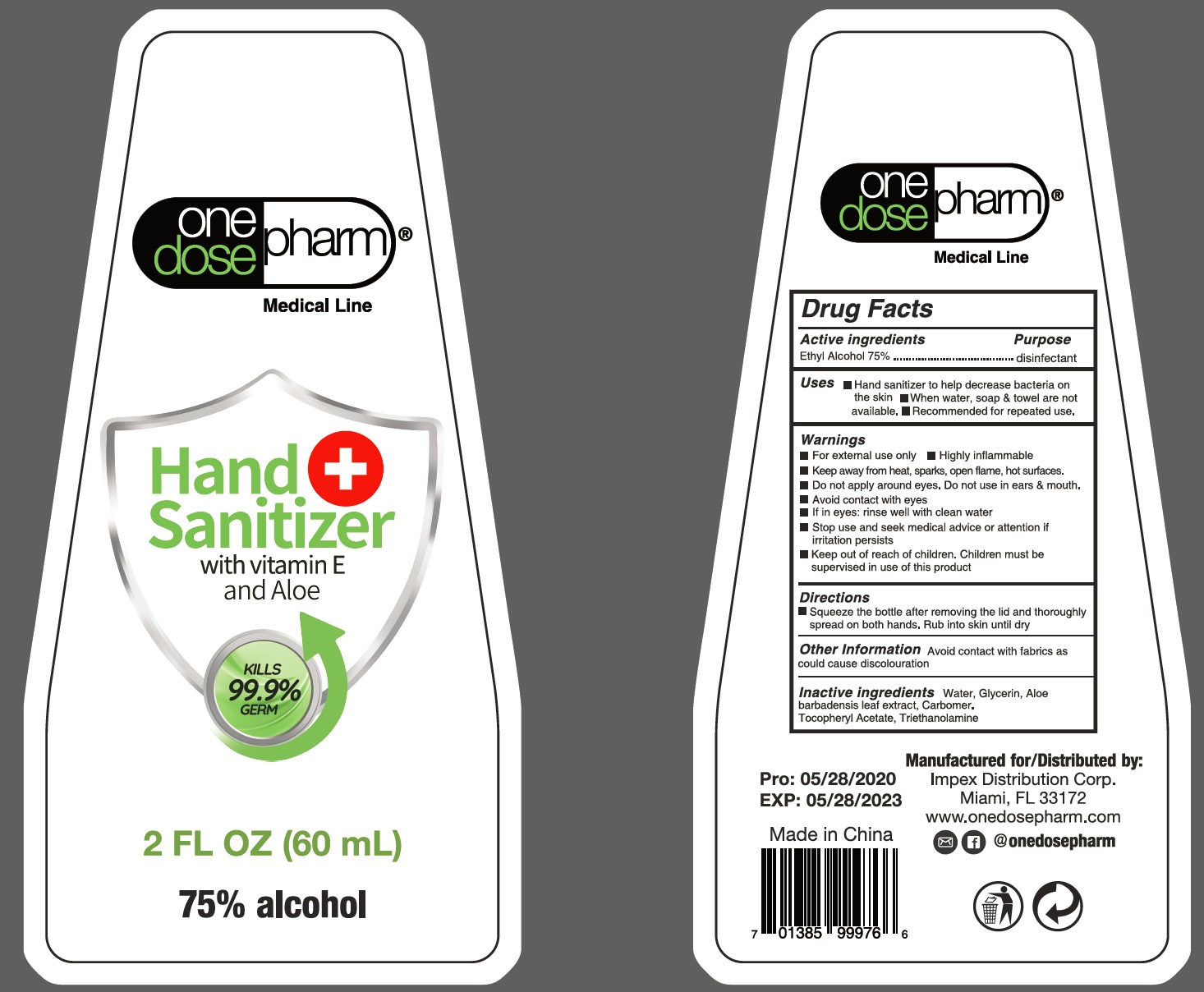 DRUG LABEL: hand sanitizer
NDC: 73788-004 | Form: GEL
Manufacturer: Hangzhou Huiji Biotechnology Co., Ltd.
Category: otc | Type: HUMAN OTC DRUG LABEL
Date: 20220224

ACTIVE INGREDIENTS: ALCOHOL 75 mL/100 mL
INACTIVE INGREDIENTS: WATER; GLYCERIN; ALOE VERA LEAF; TROLAMINE; CARBOMER 934; .ALPHA.-TOCOPHEROL ACETATE

73788-004 75% alcohol hand sanitizer gel

Active Ingredient

Ethyl Alcohol 75%

Purpose

disinfectant

Use

■ Hand sanitizer to help decrease bacterial on
the skin
■When water, soap & towel are not
available.
■Recommended for repeated use,

WARNINGS

For external use only■Highly inflammable
Keep away from heat, sparks, open flame, hot surfaces.
Do not apply around eyes. Do not use in ears & mouth.
Avoid contact with eyes
If in eyes: rinse well with clean water
Stop use and seek medical advice or attention if
irritation persists

Keep out of reach of children. Children must be
supervised in use of this product

Directions

■Squeeze the bottle after removing the lid and thoroughly
spread on both hands. Rub into skin until dry
Other Information Avoid contact with fabrics as
could cause discolouration

Inactive ingredients

Water, Glycerin, Aloe
barbadensis leaf extract, Carbomer.
Tocopheryl Acetate, Triethanolamine